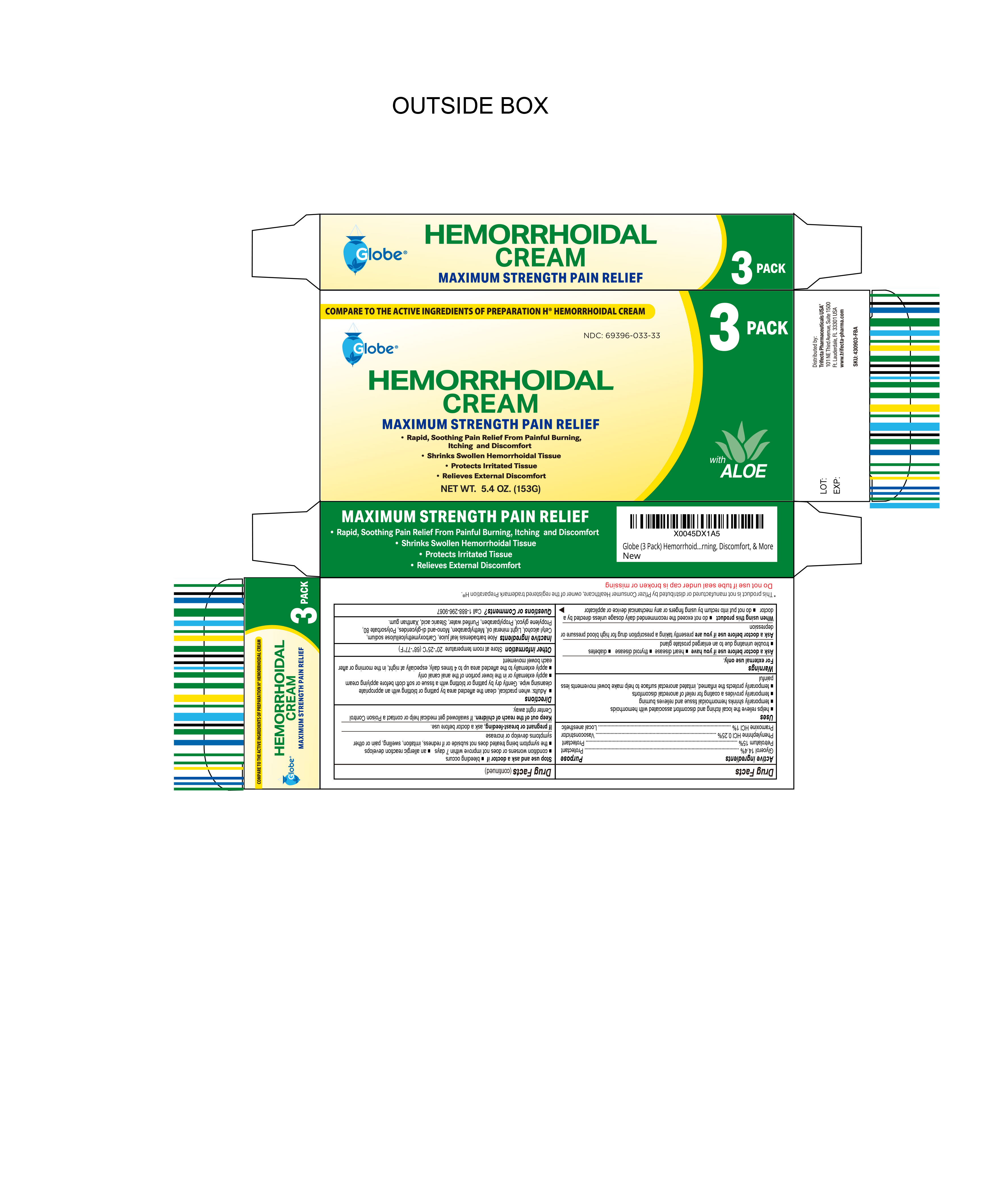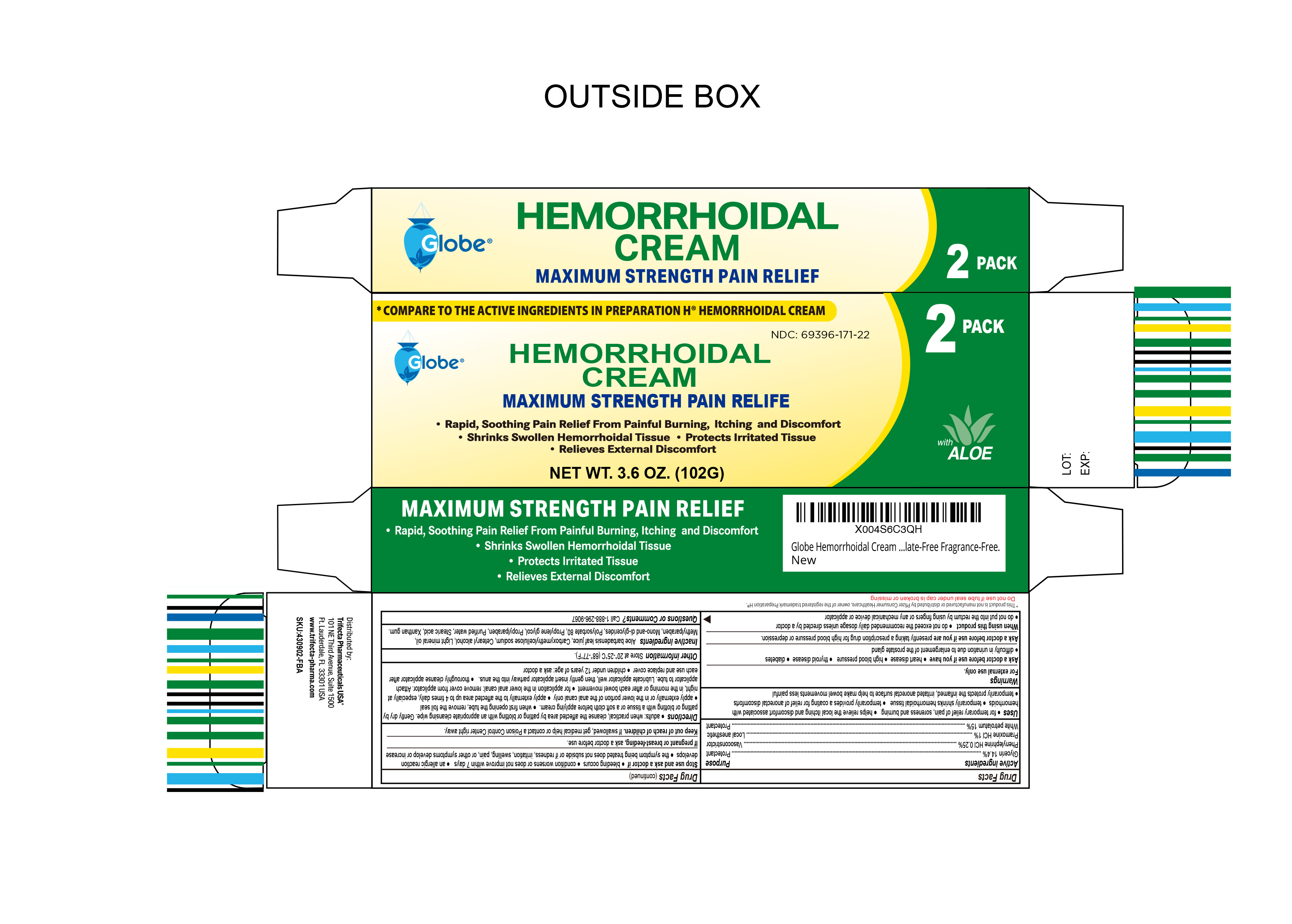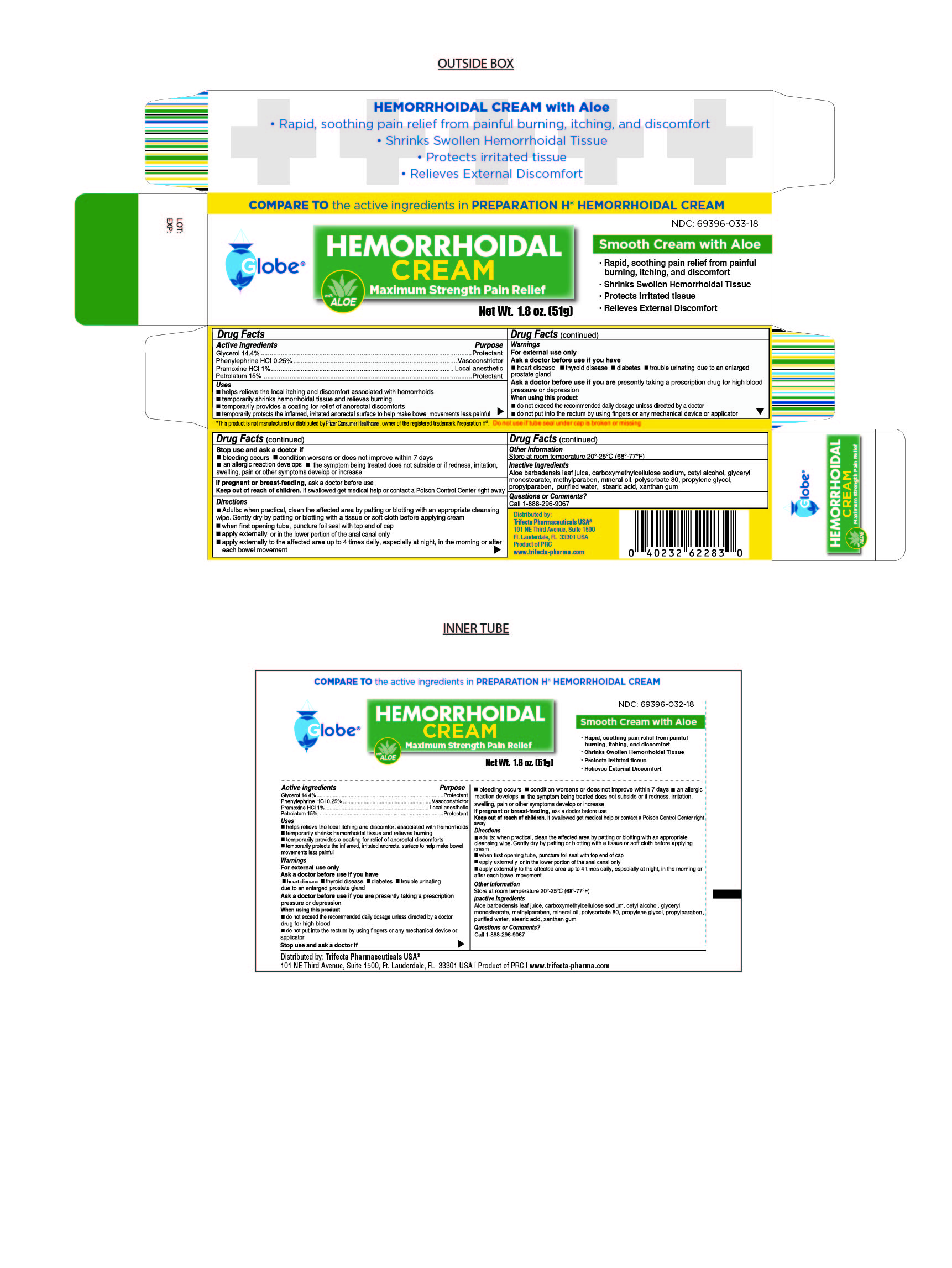 DRUG LABEL: Hemorrhoidal Cream
NDC: 69396-033 | Form: CREAM
Manufacturer: Trifecta Pharmaceuticals Usa Llc
Category: otc | Type: HUMAN OTC DRUG LABEL
Date: 20251118

ACTIVE INGREDIENTS: PRAMOXINE HYDROCHLORIDE 1 g/100 g; PETROLATUM 15 g/100 g; GLYCERIN 14.4 g/100 g; PHENYLEPHRINE HYDROCHLORIDE 0.25 g/100 g
INACTIVE INGREDIENTS: ALOE VERA LEAF; GLYCERYL MONOSTEARATE; CARBOXYMETHYLCELLULOSE SODIUM (0.7 CARBOXYMETHYL SUBSTITUTION PER SACCHARIDE; 100-200 MPA.S AT 1%); CETYL ALCOHOL; PROPYLPARABEN; MINERAL OIL; POLYSORBATE 80; PROPYLENE GLYCOL; WATER; STEARIC ACID; XANTHAN GUM; METHYLPARABEN

Hemorrhoidal Cream Maximum Strength Pain Relief

Active Ingredient

Glycerol 14.4%

Purpose

Protectant

Active Ingredient

Phenylephrine HCI 0.25%

Purpose

Vasoconstrictor

Active Ingredient

Pramoxine HCI 1%

Purpose

Local Anesthetic

Active Ingredient

Petrolatum 15%

Purpose

Protectant

Uses

Helps relieve the local itching and discomfort associated with hemorrhoids

Temporarily shrinks hemorrhoidal tissue and relieves burning

Temporarily provides a coating for relief of anorectal discomforts

Temporarily protects the inflamed, irritated anorectal surface to help make bowel movements less painful

Stop use and ask a doctor

Bleeding occurs

Condition worsens or does not improve within 7 days

An allergic reaction develops

The symptom being treated does not subside or if redness, irritation, swelling, pain or other symptoms develop or increase

If Pregnant or Breast Feeding

Ask doctor before use

Keep out of reach of children

If swallowed get medical help or contact a Poison Control Center right away

Directions

Adults:

When practical, clean the affected area by patting or blotting with an appropriate cleaning wipe. Gently dry by patting or blotting with a tissue or soft cloth before applying cream.

When first opening tube, puncture foil seal with top end of cap

Apply externally or in the lower portion of the anal canal only

Apply externally to the affected area up to 4 times daily, especially at night, in the morning or after each bowel movement

Warnings

For External Use Only

Ask doctor brfore use if you have

Heart Disease

Thyroid Disease

Diabetes

Trouble urinating due to an enlarged prostate gland

Ask doctor before use if you are presently taking a prescription for high blood pressure or depression

When using this product

Do not exceed the recommended daily dosage unless directed by a doctor

Do not put into the rectum by using fingers or any mechanical device or applicator

Other Information

Store at room temperature 20º-25ºC (68º-77ºF)

Do not use if tube seal is broken or missing

This product is not manufactured or distributed by Pfizer Consumer Healthcare, owner of the registered trademark Preparation H®

Inactive Ingredients

Aloe barbadensis leaf juice, carboxmethylcellulose sodium, cetyl alcohol, glyceryl monostearate, methylparaben, mineral oil, polysorbate 80, propylene glycol, propylparaben, purified water, stearic acid, xanthan gum

Questions or Comments

Call 1-888-296-9067

Distributed By

Trifecta Pharmaceuticals USA™

101 NE Third Avenue, Suite 1500

Ft. Lauderdale, FL. 33301, USA

1-888-296-9067

Product of PRC

www.trifecta-pharma.com